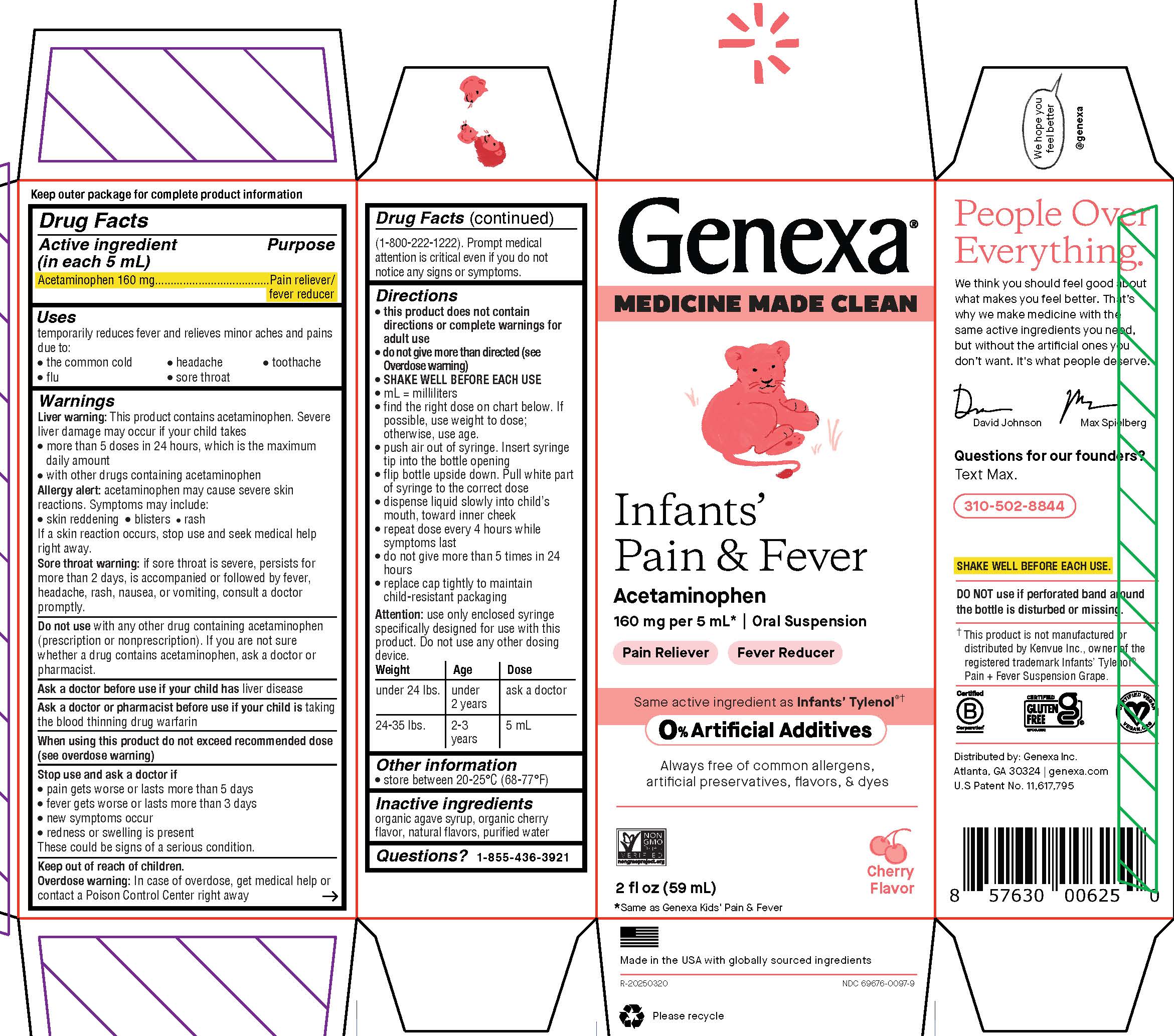 DRUG LABEL: Infants Pain and Fever Cherry Flavor
NDC: 69676-0097 | Form: SUSPENSION
Manufacturer: Genexa Inc.
Category: otc | Type: HUMAN OTC DRUG LABEL
Date: 20251125

ACTIVE INGREDIENTS: ACETAMINOPHEN 160 mg/5 mL
INACTIVE INGREDIENTS: AGAVE TEQUILANA JUICE; WATER; CHERRY

Infants' Pain & Fever Cherry Flavor

Drug Facts

Active ingredient

(in each 5 mL)

Acetaminophen 160 mg

Purpose

Pain reliever/fever reducer

Uses

temporarily reduces fever and relieves minor aches and pains due to:

- the common cold
- headache
- toothache
- flu
- sore throat

Warnings

Liver warning: This product contains acetaminophen. Severe liver damage may occur if your child takes

- more than 5 doses in 24 hours, which is the maximum daily amount
- with other drugs containing acetaminophen

Allergy alert: acetaminophen may cause severe skin reactions.

Symptoms may include:

- skin reddening
- blisters
- rash

If a skin reaction occurs, stop use and seek medical help right away.

Sore throat warning: if sore throat is severe, persists for more than 2 days, is accompanied or followed by fever, headache, rash, nausea, or vomiting, consult a doctor promptly.

Do not use with any other drug containing acetaminophen (prescription or nonprescription). If you are not sure whether a drug contains acetaminophen, ask a doctor or pharmacist.

Ask a doctor before use if your child has liver disease

Ask a doctor or pharmacist before use if your child is taking the blood thinning drug warfarin

When using this product do not exceed recommended dose (see overdose warning)

Stop use and ask a doctor if

- pain gets worse or lasts more than 5 days
- fever gets worse or lasts more than 3 days
- new symptoms occur
- redness or swelling is present

These could be signs of a serious condition

Keep out of reach of children.

OVERDOSAGE

Overdose warning: In case of overdose, get medical help or contact a Poison Control Center right away (1-800-222-1222). Prompt medical attention is critical even if you do not notice any signs or symptoms.

Directions

- this product does not contain directions or complete warnings for adult use
- do not give more than directed (see Overdose warning)
  - SHAKE WELL BEFORE EACH USE
  - mL = milliliters
  - find the right dose on chart below. If possible, use weight to dose; otherwise, use age.
  - push air out of syringe. Insert syringe tip into the bottle opening
  - flip bottle upside down. Pull white part of syringe to the correct dose
  - dispense liquid slowly into child's mouth, toward inner cheek
  - repeat dose every 4 hours while symptoms last
  - do not give more than 5 times in 24 hours
  - replace cap tightly to maintain child-resistant packaging

Attention: use only enclosed syringe specifically designed for use with this product. Do not use any other dosing device.

Weight | Age | Dose
under 24 lbs | under 2 years | ask a doctor
24-35 lbs. | 2-3 years | 5 mL

Other information

- store between 20-25°C (68-77°F)

Inactive ingredients

organic agave syrup, organic cherry flavor, natural flavors, purified water

Questions? 1-855-436-3921

SHAKE WELL BEFORE EACH USE

DO NOT use if perforated band around the bottle is disturbed or missing.

†This product is not manufactured or distributed by Kenvue Inc., owner of the registered trademark Infants' Tylenol® Pain + Fever Suspension Grape.

Distributed by: Genexa Inc.

Atlanta, GA 30324 | genexa.com

U.S.Patent No. 11,617,795

Made in the USA with globally sourced ingredients

NDC 69676-0097-9

Directions

- this product does not contain directions or complete warnings for adult use
- do not give more than directed (see Overdose warning)
- SHAKE WELL BEFORE EACH USE
- mL = milliliters
- find the right dose on chart below. If possible, use weight to dose; otherwise, use age.
- push air out of syringe. Insert syringe tip into the bottle opening
- flip bottle upside down. Pull white part of syringe to the correct dose
- dispense liquid slowly into child's mouth, toward inner cheek
- repeat dose every 4 hours while symptoms last
- do not give more than 5 times in 24 hours
- replace cap tightly to maintain child-resistant packaging

Attention: use only enclosed syringe specifically designed for use with this product. Do not use any other dosing device.

Weight | Age | Dose
under 24 lbs. | under 2 years | ask a doctor
24-35 lbs. | 2-3 years | 5 mL

PACKAGE LABEL

Genexa®

MEDICINE MADE CLEAN

Infants' Pain & Fever

Acetaminophen

160 mg per 5 mL* | Oral Suspension

Pain Reliever

Fever Reducer

Same active ingredient as Infants' Tylenol®†

0% Artificial Additives

Always free of common allergens, artificial preservatives, flavors, & dyes

2 fl oz (59 mL)

*Same as Genexa Kids' Pain & Fever

Cherry Flavor